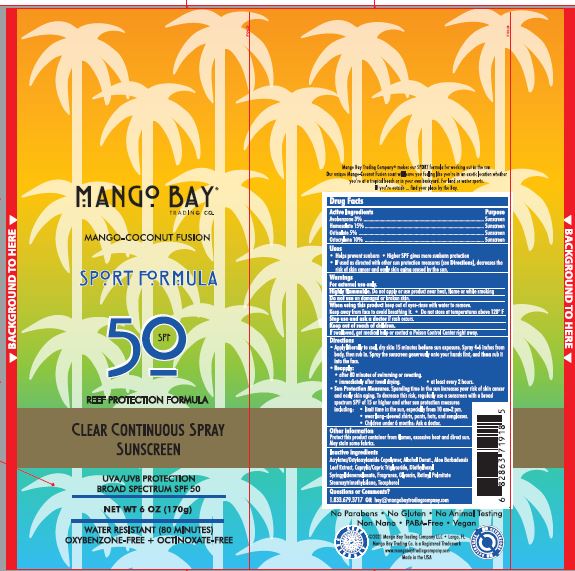 DRUG LABEL: Mango Bay SPF 50 Sport
NDC: 72667-037 | Form: SPRAY
Manufacturer: Inspec Solutions
Category: otc | Type: HUMAN OTC DRUG LABEL
Date: 20250506

ACTIVE INGREDIENTS: HOMOSALATE 15 g/100 mL; OCTOCRYLENE 10 g/100 mL; AVOBENZONE 3 g/100 mL; OCTISALATE 5 g/100 mL
INACTIVE INGREDIENTS: FRAGRANCE 13576; VITAMIN A PALMITATE; DIETHYLHEXYL SYRINGYLIDENEMALONATE; CAPRYLIC/CAPRIC/LAURIC TRIGLYCERIDE; ALOE VERA LEAF; BEHENYL BEHENATE; GLYCERIN; TOCOPHEROL; STEAROXYTRIMETHYLSILANE; ACRYLATE/ISOBUTYL METHACRYLATE/N-TERT-OCTYLACRYLAMIDE COPOLYMER (75000 MW)

Mango Bay SPF 50 Sport Sunscreen Spry

Active ingredient

Avobenzone 3.0%

Homosalate 15%

Octisalate 5%

Octocrylene 10%

When using this product:

• keep out of eyes. Rinse with water to remove.

• Keep away from face to avoid breathing it.

• Do not puncture or incinerate, Contents under pressure

• Do not store at temperature above 120⁰F

Stop use and ask a doctor if rash occurs.

PURPOSE

Avobenzone 3.0% ……………………………………………………………………………… Sunscreen

Homosalate 15.0% ……………………………………………………………………………. Sunscreen

Octisalate 5.0% …………………………………………………………………………………. Sunscreen

Octocrylene 10.0% ……………………………………………………………………………. Sunscreen

Stop use and ask a doctor if rash occurs.

Keep out of reach of children. If swallowed, get medical help or contact a Poison Control Center right away.

INACTIVE INGREDIENT

Behenyl Alcohol

BHT

Butyloctyl Salicylate

Caprylyl Methicone Dimethicone

Dimethyl Capramide

Disodium EDTA

Ethylhexyl Stearate

Ethylhexylglycerin

Fragrance

Glyceryl Stearate Hydrated Silica

PEG-100 Stearate

Phenoxyethanol

Polyester-8

Sodium Polyacrylate

Styrene/Acrylates Copolymer

Trideceth-6

Trimethylsiloxysilicate

VP/Hexadecene Copolymer

Water

Xanthan Gum

INDICATIONS AND USAGE

- Helps prevent sunburn
- Higher SPF gives more sunburn protection
- If used as directed with other sun protection measures (See Directions), decreases the risk of skin cancer and early skin aging caused by the sun.

WARNINGS

For external use only.

Highly flammable. Do not apply or use product near heat, flame or while smoking.

Do not use on damaged or broken skin.

Stop use and ask a doctor is rash occurs.

Directions

- Apply liberally to cool, dry skin 15 minutes before sun exposure. Spray 4-6 inches from body, then rub in. Spray the sunscreen generously onto your hands first, and then rub it into the face.

Reapply:

- after 80 minutes of swimming or sweating.
- immediately after towel drying.
- at least every 2 hours

Sun Protection Measures. Spending time in the sun increases your risk of skin cancer and early skin aging. To decrease this risk, regularly use a sunscreen with a broad spectrum SPF of 15 or higher and other sun protection measures including:

- limit time in the sun, especially from 10am - 2pm.
- wear long-sleeved shirts, pants, hats, and sunglasses.
- Children under 6 months: Ask a doctor.

Other information

Protect this product container from flames, excessive heat and direct sun. May stain some fabrics.

Questions or Comments?

1.833.679.3717 OR hey@mangobaytradingcompany.com